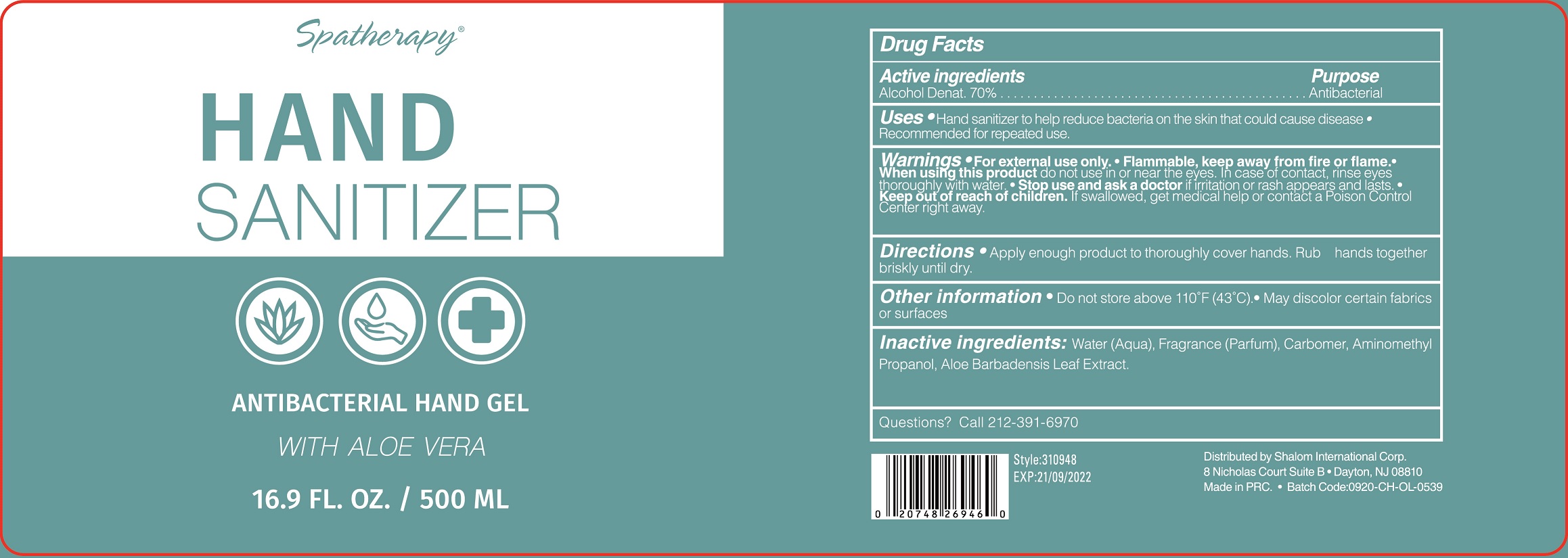 DRUG LABEL: Spatherapy Hand Sanitizer With Aloe Vera
NDC: 56136-460 | Form: GEL
Manufacturer: Ganzhou Olivee Cosmetic Co., Ltd.
Category: otc | Type: HUMAN OTC DRUG LABEL
Date: 20201020

ACTIVE INGREDIENTS: ALCOHOL 70 mL/100 mL
INACTIVE INGREDIENTS: WATER; GLYCERIN; AMINOMETHYLPROPANOL

HAND SANITIZER

Active ingredient

Alcohol Denat. 70%

Purpose

Antibacterial

Uses

- Hand Sanitizer to help reduce bacteria on the skin that could cause disease
- Recommended for repeated use.

Warnings

- For external use only.
- Flammable.Keep product away from fire or flame.
- When using this product do not use in or near the eyes. In case of contact, rinse eyes thoroughly with water.
- Stop use and ask a doctor if irritation or rash appears and lasts.

Keep out of reach of children.

If swallowed, get medical help or contact a Poison Control Center right away.

Directions

- Apply enough products to thoroughly cover hands Rub hands together briskly until dry.

Inactive ingredients

Water (Aqua), Fragrance (Parfum), Carbomer, Aminomethyl Propanol, Aloe Barbadensis Leaf Extract.

Question?

Call 212-391-6970